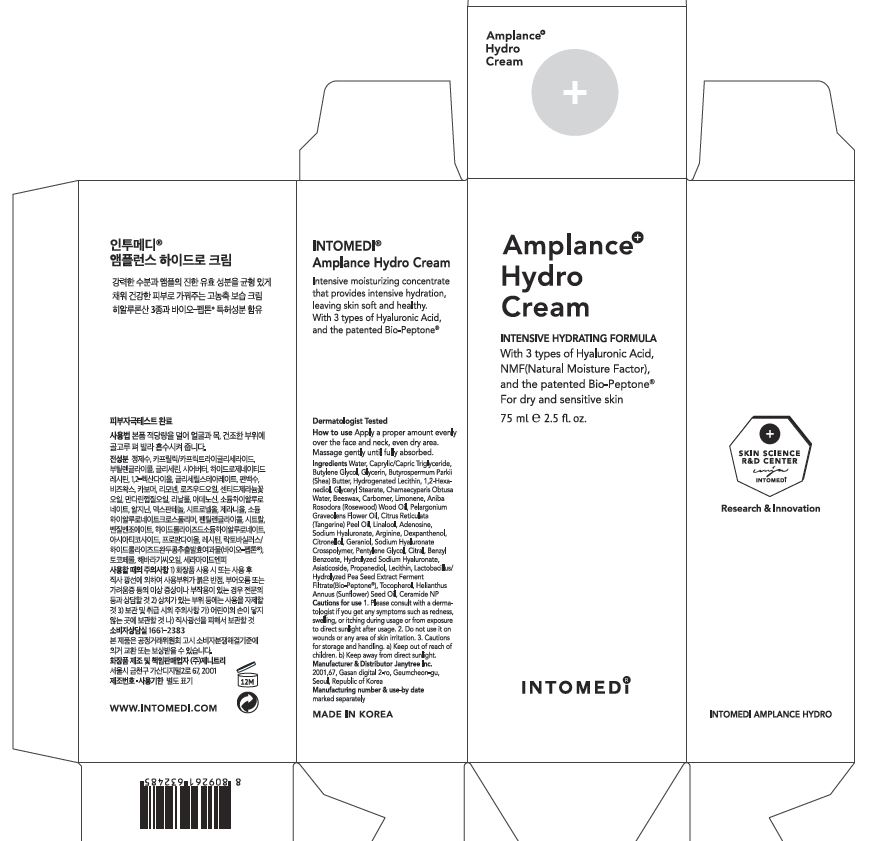 DRUG LABEL: INTOMEDI Amplance HydroCream
NDC: 82879-0002 | Form: CREAM
Manufacturer: Janytree Inc.
Category: otc | Type: HUMAN OTC DRUG LABEL
Date: 20220712

ACTIVE INGREDIENTS: ADENOSINE 0.1 g/100 mL
INACTIVE INGREDIENTS: WATER; ARGININE

INACTIVE INGREDIENTS

water, arginine, tocopherol etc.

ACTIVE INGREDIENTS

adenosine

PURPOSE

intensive hydrating ampoule for healthy, balanced skin

WARNINGS

For external use only When using this product
■ If following abnormal symptoms occurs after using the product, stop using the product and consult with a skin specialist. Symptoms : Red specks, swelling, itching
■ Do not use on the skin parts affected by wound, eczema, or dermatitis.
Keep out of reach of children.
■ If swallowed, get a medical help or contact a person in control center immediately.
■ Avoid contact with eyes.

KEEP OUT OF REACH OF CHILDREN

If swallowed, get a medical help or contact a person in control center immediately.

INDICATIONS AND USAGE

apply a properamount to the skin, and massage gently until fully absorbed

DOSAGE AND ADMINISTRATION

for external use only